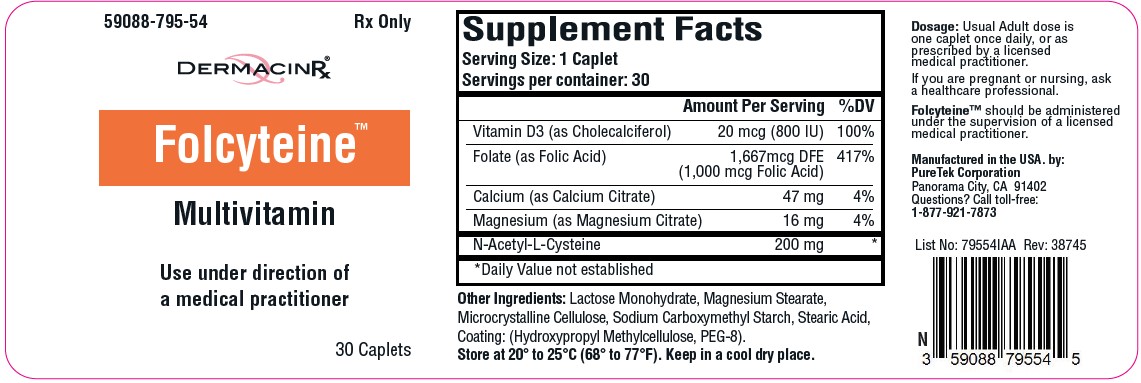 DRUG LABEL: Folcyteine
NDC: 59088-795 | Form: TABLET
Manufacturer: PureTek Corporation
Category: prescription | Type: HUMAN PRESCRIPTION DRUG LABEL
Date: 20230914

ACTIVE INGREDIENTS: CALCIUM CITRATE 47 mg/1 1; CHOLECALCIFEROL 800 [iU]/1 1; FOLIC ACID 1000 ug/1 1; ACETYLCYSTEINE 200 mg/1 1; MAGNESIUM CITRATE 16 mg/1 1
INACTIVE INGREDIENTS: STEARIC ACID; POLYETHYLENE GLYCOL 400; CELLULOSE, MICROCRYSTALLINE; SODIUM STARCH GLYCOLATE TYPE A; MAGNESIUM STEARATE; HYPROMELLOSES; LACTOSE MONOHYDRATE

Folcyteine

DESCRIPTION:

Each caplet contains:
Vitamin D3 (as Cholecalciferol) .................. 20 mcg (800 IU)
Folate (as Folic Acid)...1,667 mcg DFE (1,000 mcg Folic Acid)
Calcium (as Calcium Citrate)....................................... 47 mg
Magnesium (as Magnesium Citrate)........................... 16 mg
N-Acetyl-L-Cysteine................................................... 200 mg

Other Ingredients:

Lactose Monohydrate, Magnesium Stearate, Microcrystalline Cellulose, Sodium Carboxymethyl Starch, Stearic Acid, Coating: (Hydroxypropyl Methylcellulose, PEG-8).

Indications and Usage:

Folcyteine™ is indicated to provide vitamin supplement to men and women. Folic acid is effective in the treatment of megaloblastic anemias due to a deficiency of folic acid (as may be seen in tropical or nontropical sprue) and in anemias of nutritional origin, pregnancy, infancy, or childhood

Contraindications:

This product is contraindicated in patients with a known hypersensitivity to any of the ingredients. Folcyteine™ is contraindicated in patients with hypercalcemia, malabsorption syndrome, abnormal sensitivity to the toxic effects of vitamin D, and hypervitaminosis D.

Warnings:

Tell your doctor if you have: kidney problems, thyroid disease. This medication should be used as directed during pregnancy or while breast-feeding. Consult your doctor. Administration of folic acid alone is improper therapy for pernicious anemia and other megaloblastic anemias in which vitamin B12 is deficient.

Precautions

Folic acid in doses above 0.1 mg daily may obscure pernicious anemia, in that hematologic remission can occur while neurological manifestations remain progressive. There is a potential danger in administering folic acid to patients with undiagnosed anemia, since folic acid may obscure the diagnosis of pernicious anemia by alleviating the hematologic manifestations of the disease while allowing the neurologic complications to progress. This may result in severe nervous system damage before the correct diagnosis is made. The patient’s medical conditions and consumption of other drugs, herbs, and/or supplements should be considered.

For use on the order of a healthcare practitioner.

Call your doctor about side effects. To report side effects, call PureTek Corporation at 1-877-921-7873 or FDA at 1-800-FDA-1088 or www.fda.gov/medwatch.

Adverse Reactions:

Allergic sensitization has been reported following both oral and parenteral administration of folic acid.

You should call your doctor for medical advice about serious adverse events. To report adverse side effects or to obtain product information, contact PureTek Corporation, at 1-877-921-7873.

Dosage and Administration:

One (1) Folcyteine™ caplet daily or as directed by a physician. Do not administer to children under the age of 12.

How Supplied:

Folcyteine™ are pale yellow, clear coated caplets in bottles containing 30 caplets – NDC 59088-795-54. Dispense in a tight, light-resistant container as defined in the USP/NF with a child resistant closure.

Storage

Do not use if bottle seal is broken.

KEEP THIS AND ALL MEDICATIONS OUT OF THE REACH OF CHILDREN.

Store at controlled room temperature 20° to 25°C (68° to 77°F). [See USP]. Protect from light and moisture and avoid excessive heat.

To report a serious adverse event or to obtain product information, contact 877-921-7873.

Manufactured by:

PureTek Corporation Panorama City, CA 91402

For questions or information call toll-free: 877-921-7873

Folcyteine™

Manufactured in the USA by:
PureTek Corporation
Panorama City, CA 91402
For questions or information
call toll-free: 877-921-7873